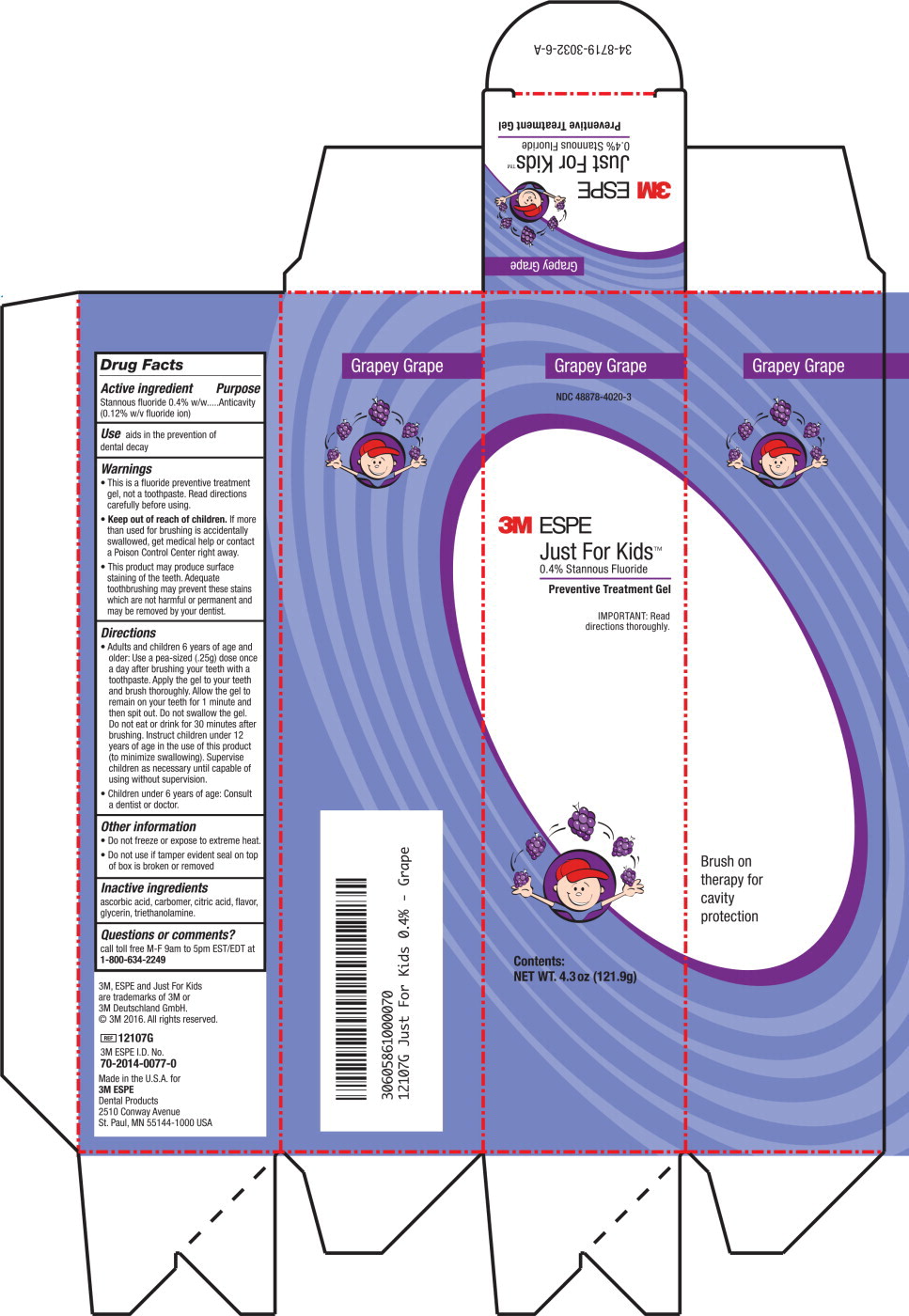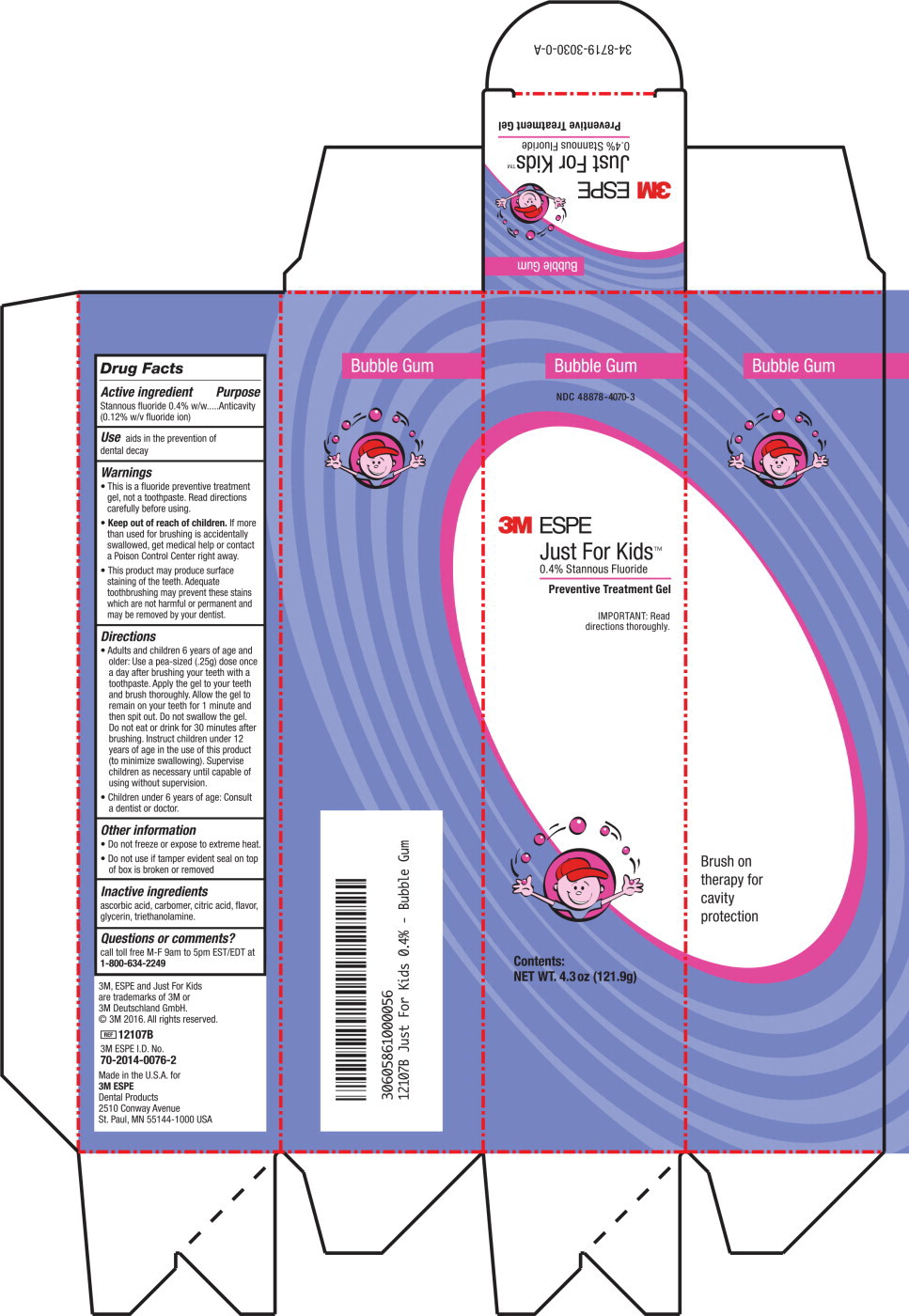 DRUG LABEL: Just For Kids
NDC: 48878-4020 | Form: GEL
Manufacturer: Solventum US LLC
Category: otc | Type: HUMAN OTC DRUG LABEL
Date: 20240801

ACTIVE INGREDIENTS: Stannous Fluoride 0.969 mg/1 g
INACTIVE INGREDIENTS: Ascorbic Acid; Carbomer Homopolymer Type B (Allyl Sucrose Crosslinked); Anhydrous Citric Acid; Glycerin; Trolamine

Just For Kids

Drug Facts

Active ingredient

Stannous fluoride 0.4% w/w (0.12% w/f fluoride ion)

Purpose

Anticavity

Use

Aids in the prevention of dental decay

Warnings

KEEP OUT OF REACH OF CHILDREN

- This is a fluoride preventive treatment gel, not a toothpaste. Read directions carefully before using.
- Keep out of reach of children. If more than used for brushing is accidentally swallowed, gel medical help or contact a Poison Control Center right away.
- This product may produce surface staining of the teeth. Adequate toothbrushing may prevent these stains which are not harmful or permanent and may be removed by your dentist.

Directions

- Adults and children 6 years of age and older: Use a pea-sized (.25g) dose once a day after brushing your teeth with a toothpaste. Apply the gel to your teeth and brush thoroughly. Allow the gel to remain on your teeth for 1 minute and then spit out. Do not swallow the gel. Do not eat or drink for 30 minutes after brushing. Instruct children under 12 years of age in the use of this product (to minimize swallowing). Supervise children as necessary until capable of using without supervision.
- Children under 6 years of age: Consult a dentist or doctor.

Other information

- Do not freeze or expose to extreme heat.
- Do not use if tamper evident seal on top of box is broken or removed.

Inactive ingredients

ascorbic acid, carbomer, citric acid, flavor, glycerin, triethanolamine

Questions or comments?

call toll free M-F 9am to 5pm EST/EDT at 1-800-634-2249

Principle Display Panel - Grape

Grapey Grape

NDC 48878-4020-3

3M ESPE

Just For Kids™

0.4% Stannous Fluoride

Preventive Treatment Gel

IMPORTANT: Read

directions thoroughly.

Contents:

NET WT. 4.3 oz (121.9 g)

Principle Display Panel - Bubble Gum

Bubble Gum

NDC 48878-4070-3

3M ESPE

Just For Kids™

0.4% Stannous Fluoride

Preventive Treatment Gel

IMPORTANT: Read

directions thoroughly.

Contents:

NET WT. 4.3 oz (121.9 g)